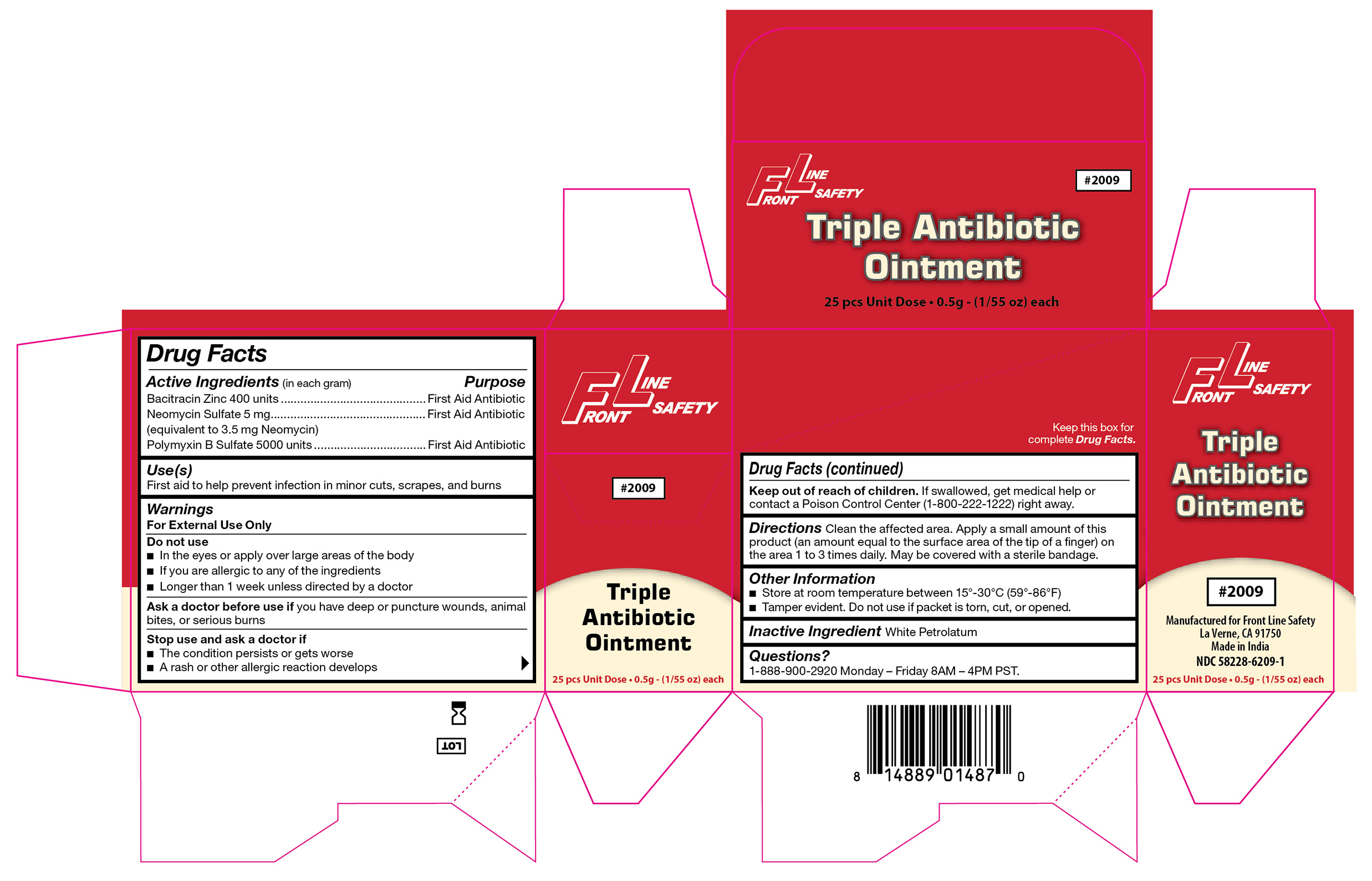 DRUG LABEL: Triple Antibiotic
NDC: 58228-6209 | Form: OINTMENT
Manufacturer: Front Line Safety
Category: otc | Type: HUMAN OTC DRUG LABEL
Date: 20251215

ACTIVE INGREDIENTS: BACITRACIN ZINC 400 [iU]/1 g; NEOMYCIN SULFATE 5 mg/1 g; POLYMYXIN B SULFATE 5000 [iU]/1 g
INACTIVE INGREDIENTS: WHITE PETROLATUM

FL-2009

Active Ingredient (in each gram)

Bacitracin Zinc 400 units

Purpose

First Aid Antibiotic

Active Ingredient (in each gram)

Neomycin Sulfate 5 mg (equivalent to 3.5 mg Neomycin)

Purpose

First Aid Antibiotic

Active Ingredient (in each gram)

Polymyxin B Sulfate 5000 units

Purpose

First Aid Antibiotic

Use(s)

First aid to help prevent infection in minor cuts, scrapes, and burns

Warnings

For External Use Only

Do not use

• In the eyes or apply over large areas of the body

• If you are allergic to any of the ingredients

• Longer than 1 week unless directed by a doctor

Ask a doctor before use if

You have deep or puncture wounds, animal bites, or serious burns

Stop use and ask a doctor if

• The condition perists or gets worse

• A rash or other allergic reaction develops

Keep out of reach of children

If swallowed, get medical help or contact a Poison Control Center (1-800-222-1222) right away.

Directions

Clean the affected area. Apply a small amount of this product (an amount equal to the surface area of the tip of a finger) on the area 1 to 3 times daily. May be covered with a sterile bandage.

Other Information

• Store at room temperature between 15º-30ºC (59º-86ºF)

• Tamper evident. Do not use if packet is torn, cut, or opened.

Inactive Ingredient

White Petrolatum

Questions?

1-888-900-2920 Monday - Friday 8AM-4PM PST.

Label

FL-2009